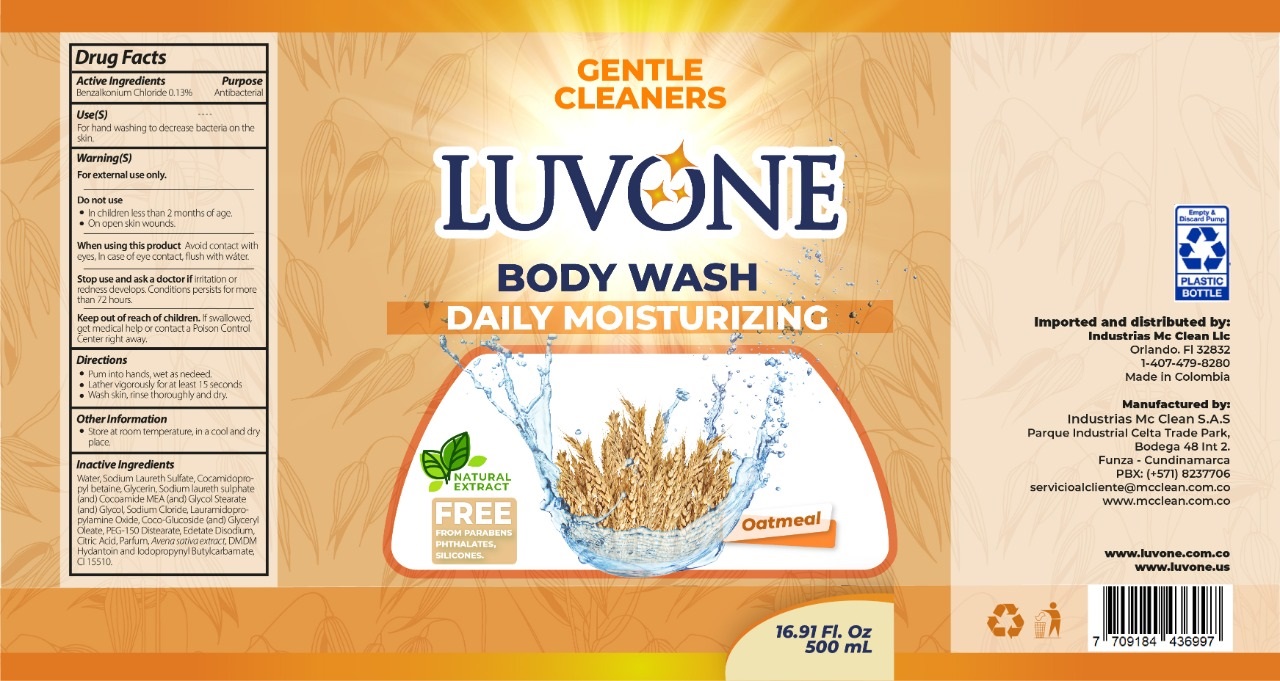 DRUG LABEL: Luvone Body Wash Daily Moisturizing Oatmeal
NDC: 80683-002 | Form: LIQUID
Manufacturer: INDUSTRIAS MC CLEAN S A S
Category: otc | Type: HUMAN OTC DRUG LABEL
Date: 20210713

ACTIVE INGREDIENTS: BENZALKONIUM CHLORIDE 1.3 mg/1 mL
INACTIVE INGREDIENTS: WATER; SODIUM LAURETH SULFATE; COCAMIDOPROPYL BETAINE; GLYCERIN; COCO MONOETHANOLAMIDE; GLYCOL STEARATE; SODIUM CHLORIDE; LAURAMIDOPROPYLAMINE OXIDE; COCO GLUCOSIDE; GLYCERYL OLEATE; PEG-150 DISTEARATE; EDETATE DISODIUM; CITRIC ACID MONOHYDRATE; AVENA SATIVA FLOWERING TOP; DMDM HYDANTOIN; IODOPROPYNYL BUTYLCARBAMATE; D&C ORANGE NO. 4

Luvone Body Wash Daily Moisturizing Oatmeal

Active Ingredients

Benzalkonium Chlorie 0.13%

Purpose

Antibacterial

Use(S)

For hand washing to decrease bacteria on the skin.

Warning(S)

For external use only.

Do not use

- In children less than 2 months of age.
- On open skin wounds.

When using this product

Avoid contact with eyes. In case of eye contact, flush with water.

Stop use and ask a doctor if

irritation or redness develops. Conditions persists for more than 72 hours.

Keep out of reach of children.

If swallowed, get medical help or contact a Poison Control Center right away.

Directions

- Pum into hands, wet as nedeed.
- Lather vigorously for at least 15 seconds
- Wash skin, rinse thoroughly and dry.

Other Information

- Store at room temperature, in a cool and dry place.

Inactive Ingredients

Water, Sodium Laureth Sulfate, Cocamidopropyl betaine, Glycerin, Sodium laureth sulphate (and) Cocoamido MEA (and) Glycol Stearate (and) Gycol, Sodium Chloride, Lauramidopropylamine Oxide, Coco-Glucoside (and) Glyceryl Oleate, PEG-150 Distearate, Edetate Disodium, Citric Acid, Parfum, Avena sativa extract, DMDM Hydantoin and Iodopropynyl Butylcarbamate, CI 15510.